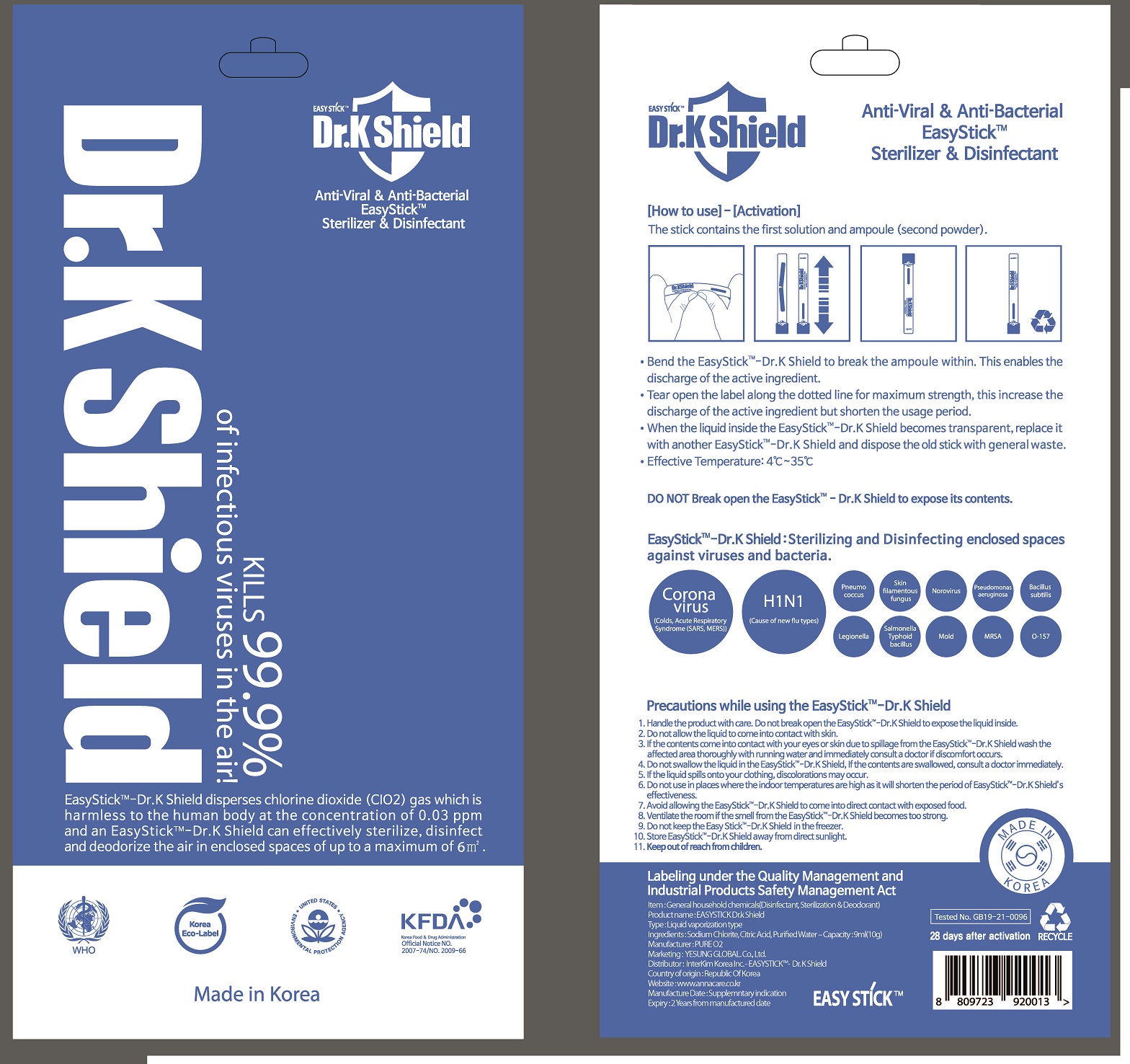 DRUG LABEL: EASYSTICK Dr.k shield
NDC: 81468-0004 | Form: LIQUID
Manufacturer: YESUNG GLOBAL.Co.,Ltd
Category: otc | Type: HUMAN OTC DRUG LABEL
Date: 20210215

ACTIVE INGREDIENTS: SODIUM CHLORITE 5 g/100 g
INACTIVE INGREDIENTS: CITRIC ACID MONOHYDRATE; SODIUM BISULFATE

Drug Facts

ACTIVE INGREDIENT

sodium chlorite

INACTIVE INGREDIENT

citric acid, sodium bisulfate

PURPOSE

anti bacteria, virus, odors

KEEP OUT OF REACH OF THE CHILDREN

INDICATIONS AND USAGE

please see the label attached

WARNINGS

■ For external use only.

■ Do not use in eyes.

■ lf swallowed, get medical help promptly.

■ Stop use, ask doctor lf irritation occurs.

■ Keep out of reach of children.

DOSAGE AND ADMINISTRATION

for external use only